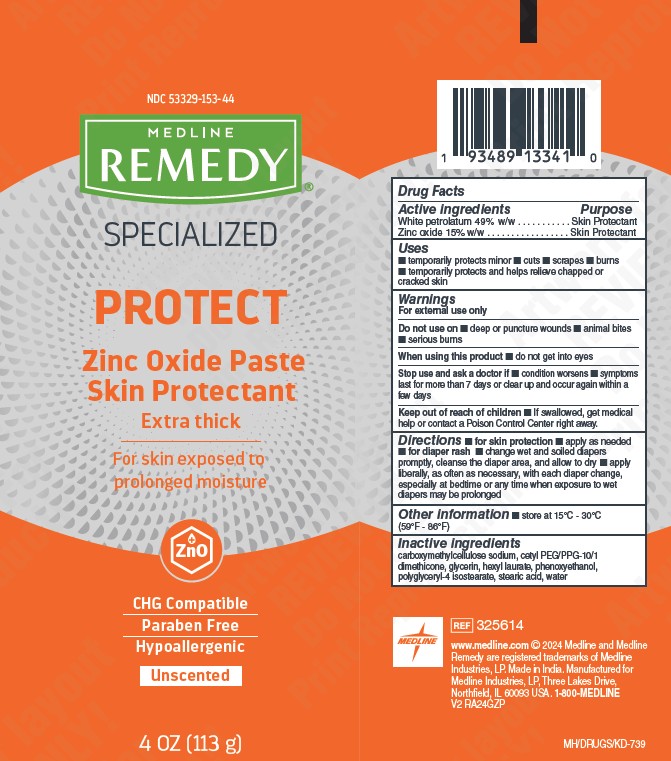 DRUG LABEL: Medline
NDC: 53329-153 | Form: PASTE
Manufacturer: Medline Industries, LP
Category: otc | Type: HUMAN OTC DRUG LABEL
Date: 20251029

ACTIVE INGREDIENTS: ZINC OXIDE 150 mg/1 g; WHITE PETROLATUM 490 mg/1 g
INACTIVE INGREDIENTS: HEXYL LAURATE; CETYL PEG/PPG-10/1 DIMETHICONE (HLB 5); POLYGLYCERYL-4 ISOSTEARATE; GLYCERIN; STEARIC ACID; CARBOXYMETHYLCELLULOSE SODIUM; WATER; PHENOXYETHANOL

153 Remedy Specialized Zinc Oxide Paste

Active ingredients

White petrolatum 49% w/w

Zinc oxide 15% w/w

Purpose

Skin protectant

Uses

- temporarily protects minor cuts, scrapes, and burns
- temporarily protects and helps relieve chapped or cracked skin

Warnings

For external use only

Do not use on

- deep or puncture wounds
- animal bites
- serious burns

When using this product

- do not get into eyes

Stop use and ask a doctor if

- condition worsens
- symptoms last for more than 7 days or clear up and occur again withinn a few days

Keep out of reach of children.

If swallowed, get medical help or contact a Poison Control Center right away.

Directions

- for skin protection: apply as needed
- for diaper rash: change wet and soiled diapers promptly, cleanse the diaper area, and allow to dry
- apply liberally, as often as necessary, with each diaper change, especially at bedtime or any time when exposure to wet diapers may be prolonged

Other information

- store at 15°C-30°C (59°F-86°F)

Inactive ingredients

carboxymethylcellulose sodium, cetyl PEG/PPG-10/1 dimethicone, glycerin, hexyl laurate, phenoxyethanol, polyglyceryl-4 isostearate, stearic acid, water

Manufacturing Information

www.medline.com

©2024 Medline and Medline Remedy

are registered trademarks of

Medline Industries, LP.

Made in India.

Manufactured for Medline Industries, LP

Three Lakes Drive, Northfield, IL 60093 USA

1-800-MEDLINE

REF: 325614